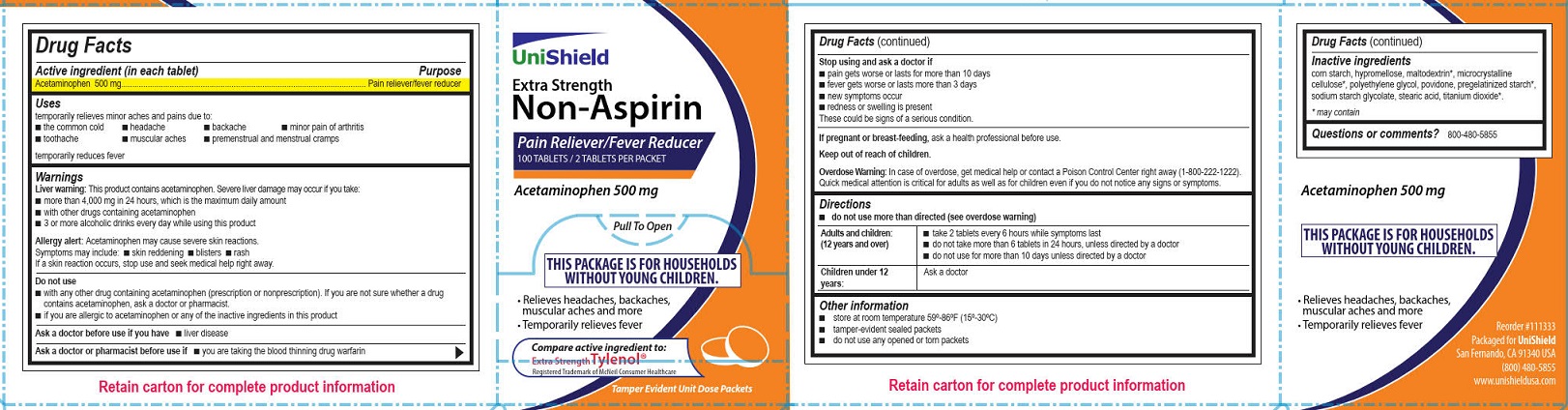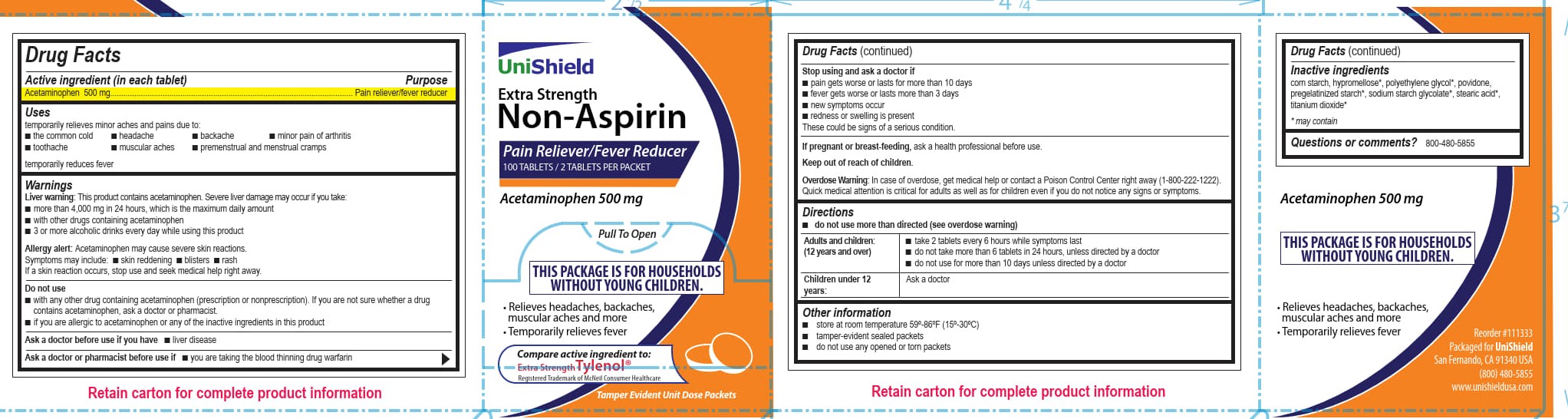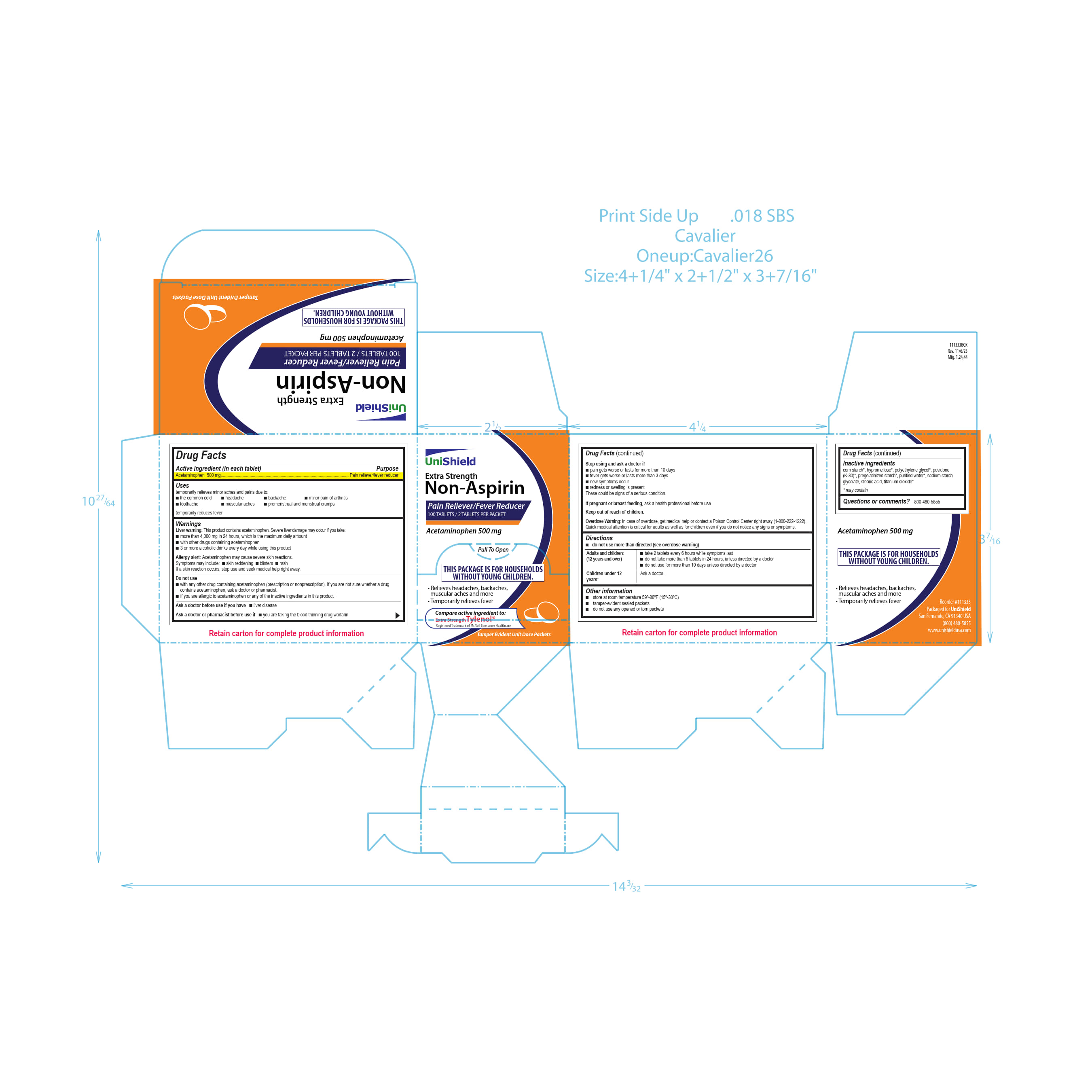 DRUG LABEL: Unishield Extra Strength Non-Aspirin
NDC: 49314-1773 | Form: TABLET
Manufacturer: Unishield
Category: otc | Type: HUMAN OTC DRUG LABEL
Date: 20260119

ACTIVE INGREDIENTS: ACETAMINOPHEN 500 mg/1 1
INACTIVE INGREDIENTS: STEARIC ACID; STARCH, CORN; SODIUM STARCH GLYCOLATE TYPE A POTATO; POVIDONE, UNSPECIFIED

Unishield Extra Strength Non-Aspirin

Drug Facts

Active ingredient (in each tablet)

Acetaminophen 500 mg.

Purpose

Pain reliever/fever reducer

Uses

temporarily relieves minor aches and pains due to:

■ headache

■ muscular aches

■ backache

■ minor pain of arthritis

■ the common cold

■ toothache

■ premenstrual and menstrual cramps

temporarily reduces fever

Warnings

Liver warning: This product contains acetaminophen. Severe liver damage may occur if you take:

■ more than 4,000 mg in 24 hours, which is the maximum daily amount

■ with other drugs containing acetaminophen

■ 3 or more alcoholic drinks every day while using this product

Allergy alert: Acetaminophen may cause severe skin reactions. Symptoms may include:

■ skin reddening

■ blisters

■ rash

If a skin reaction occurs, stop use and seek medical help right away.

Do not use

■ with any other drug containing acetaminophen (prescription or nonprescription). If you are not sure whether a
drug contains acetaminophen, ask a doctor or pharmacist.

■ if you are allergic to acetaminophen or any of the inactive ingredients in this product

Ask a doctor before use if you have

■ liver disease

Ask a doctor or pharmacist before use if

■ you are taking the blood thinning drug warfarin

Stop using and ask a doctor if

■ pain gets worse or lasts more than for more than 10 days

■ fever gets worse or lasts more than 3 days

■ new symptoms occur

■ redness or swelling is present

These could be signs of a serious condition.

PREGNANCY OR BREAST FEEDING

If pregnant or breast-feeding, ask a health professional before use.

Keep out of reach of children.

Overdose Warning:

In case of overdose, get medical help or contact a Poison Control Center right away (1-800-222-1222). Quick medical attention is critical for adults as well as for children even if you do not notice any signs or symptoms.

Directions

■ do not use more than directed (see overdose warning)

Adults and children 12 years and over

■ take 2 tablets every 6 hours while symptoms last.
■ do not take more than 6 tablets in 24 hours, unless directed by a doctor

■ do not use for more than 10 days unless directed by a doctor

Children under 12 years Ask a doctor

Other information

■ store at room temperature 59º-86ºF (15º-30ºC)

■ tamper-evident sealed packets

■ do not use any opened or torn packets

Inactive ingredients

corn starch*, hypromellose*, polyethylene glycol*, povidone (K-30)*, pregelatinized starch*, purified water*, sodium starch glycolate, stearic acid*, titanium dioxide*.

* may contain

Questions or comments? 800-480-5855

Unishield Extra Strength Non-Aspirin

Unishield

Extra Strength

Non-Aspirin

Pain Reliever/Fever Reducer

100 Tablets/2Tablets Per Packet

Acetaminophen 500 mg

Pull To Open

This Package is for Households Without Young Children.

• Relieves headaches, backaches, muscular aches and more

• Temporarily relieves fever

Compare active ingredients to:

Extra Strength Tylenol®

Registered Trademark of McNeil Consumer Healthcare

Tamper Evident Unit Dose Packets

Unishield Extra Strength Non-Aspirin Label

Unishield

Extra Strength

Non-Aspirin

Pain Reliever/Fever Reducer

100 Tablets/2Tablets Per Packet

Acetaminophen 500 mg

Pull To Open

This Package is for Households Without Young Children.

• Relieves headaches, backaches, muscular aches and more

• Temporarily relieves fever

Compare active ingredients to:

Extra Strength Tylenol®

Registered Trademark of McNeil Consumer Healthcare

Tamper Evident Unit Dose Packets